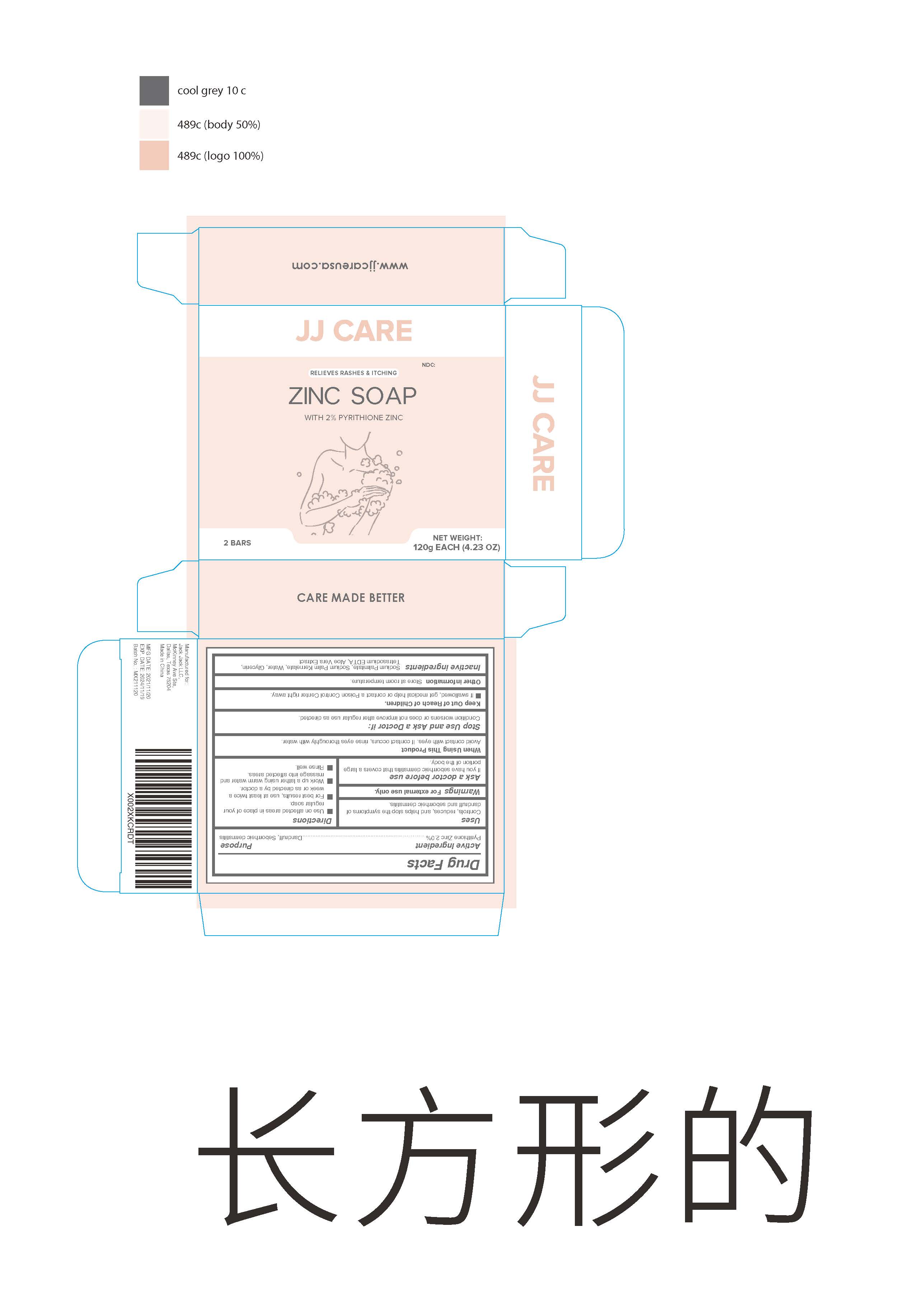 DRUG LABEL: Zinc
NDC: 78565-007 | Form: SOAP
Manufacturer: Meixin Beauty & Health Care Products Co., Ltd.
Category: otc | Type: HUMAN OTC DRUG LABEL
Date: 20220402

ACTIVE INGREDIENTS: PYRITHIONE ZINC 2 g/100 g
INACTIVE INGREDIENTS: EDETATE SODIUM; SODIUM PALMITATE; SODIUM PALM KERNELATE; ALOE VERA LEAF; WATER; GLYCERIN

78565-007
Zinc soap

Active Ingredient(s)

Pyrithione Zinc 2.0%

Purpose

Dandruff, Seborrheic dermatitis

Warnings

For external use only

Do not use

Avoid contact with eyes

When using this product Avoid contact with eyes. If contact occurs , rinse eyes thoroughly with water

Stop Use and Ask a Doctor if

Condition worsens or does not improve after regular use as directed

Keep Out of Reach of Children

If swallowed , get medical help or contact a Poison Control Center right away

Directions

Use on affected areas in place of your regular soap.

For best results use at least twice a week or as directed by a doctor.

Work up a lather using warm water and massage into affected areas.

Rinse well.

Other information

Store at room temperature

Inactive ingredients

Sodium Palmitate , Sodium Palm Kernelate , Water , Glycerin ,Tetrasodium EDTA . Aloe Vera Extract

INDICATIONS AND USAGE

Controls , reduces , and helps stop the symptoms of dandruff and seborrheic dermatitis

Package Label - Principal Display Panel

120g 78565-007-01